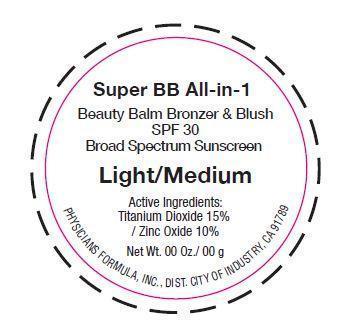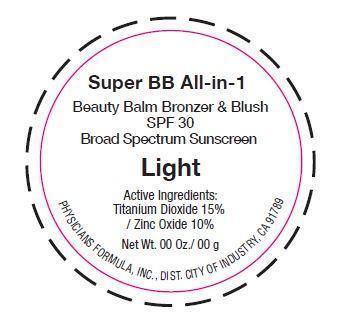 DRUG LABEL: Super BB All-In-1
NDC: 69184-001 | Form: CREAM
Manufacturer: Mei Shual Cosmetics Co., Ltd.
Category: otc | Type: HUMAN OTC DRUG LABEL
Date: 20140918

ACTIVE INGREDIENTS: TITANIUM DIOXIDE 15 mg/100 mg; ZINC OXIDE 10 1/100 mg
INACTIVE INGREDIENTS: MICA; BORON NITRIDE; WATER; ZINC STEARATE; OCTYLDODECYL STEAROYL STEARATE; LAUROYL LYSINE; DIMETHICONE; GLYCERIN; TRIETHYLHEXANOIN; DIMETHICONE/VINYL DIMETHICONE CROSSPOLYMER (SOFT PARTICLE); POTASSIUM SORBATE; SODIUM DEHYDROACETATE; .ALPHA.-TOCOPHEROL ACETATE; EGG PHOSPHOLIPIDS; TETRAHEXYLDECYL ASCORBATE; SALIX ALBA BARK; BROWN IRON OXIDE; D&C RED NO. 6; D&C RED NO. 7; ULTRAMARINE BLUE; FERRIC FERROCYANIDE

Active Ingredients:

Titanium Dioxide 15%

Zinc Oxide 10%

Purpose

Keep out of reach of children.

Warnings

Dosage & Administration

Indications & Usage

INACTIVE INGREDIENT

Titanium Dioxide, Zinc Oxide, Mica, Boron Nitride, Water, Zinc Stearate, Octyldodecyl Stearoyl Stearate, Lauroyl Lysine, Dimethicone, Glycerin, Triethylhexanoin, Vinyl Dimethicone/Methicone Silsesquioxane Crosspolymer, Potassium Sorbate, Sodium Dehydroacetate, Tocopheryl Acetate, Lecithin, Tetrahexyldecyl Ascorbate, Salix Alba(Willow) Bark Extract Powder